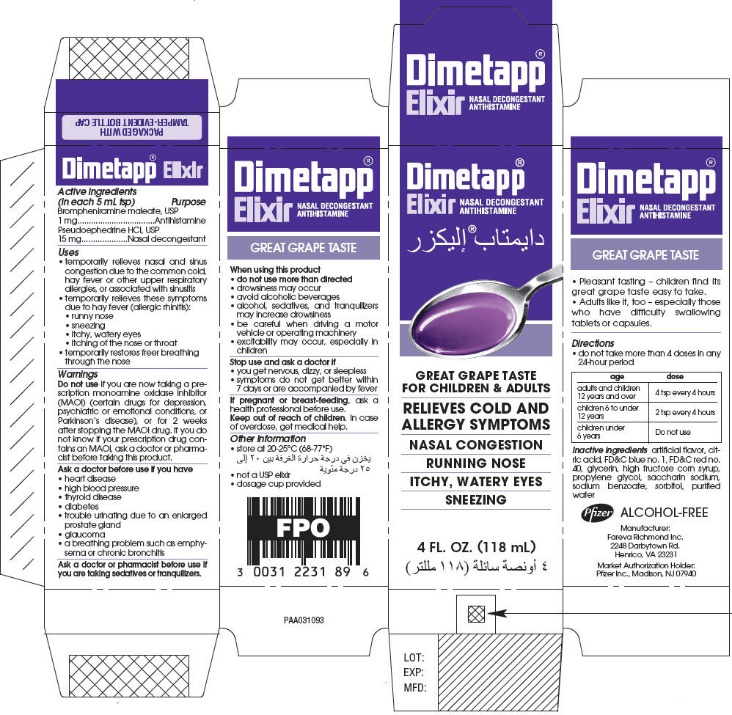 DRUG LABEL: Dimetapp
NDC: 0031-2231 | Form: ELIXIR
Manufacturer: Haleon US Holdings LLC
Category: otc | Type: HUMAN OTC DRUG LABEL
Date: 20240424

ACTIVE INGREDIENTS: BROMPHENIRAMINE MALEATE 1 mg/5 mL; PSEUDOEPHEDRINE HYDROCHLORIDE 15 mg/5 mL
INACTIVE INGREDIENTS: CITRIC ACID MONOHYDRATE; FD&C BLUE NO. 1; FD&C RED NO. 40; HIGH FRUCTOSE CORN SYRUP; SACCHARIN SODIUM; SODIUM BENZOATE; SORBITOL; WATER

Dimetapp®

ACTIVE INGREDIENT

Active ingredients (in each 5 mL tsp) | Purpose
Brompheniramine maleate, USP 1 mg | Antihistamine
Pseudoephedrine HCl, USP 15 mg | Nasal decongestant

Uses

- temporarily relieves nasal and sinus congestion due to the common cold, hay fever or other upper respiratory allergies, or associated with sinusitis
- temporarily relieves these symptoms due to hay fever (allergic rhinitis):
  - runny nose
  - sneezing
  - itchy, watery eyes
  - itching of the nose or throat
- temporarily restores freer breathing through the nose

Warnings

DO NOT USE

Do not useif you are now taking a prescription monoamine oxidase inhibitor (MAOI) (certain drugs for depression, psychiatric or emotional conditions, or Parkinson's disease), or for 2 weeks after stopping the MAOI drug. If you do not know if your prescription drug contains an MAOI, ask a doctor or pharmacist before taking this product.

Ask a doctor before use if you have

- heart disease
- high blood pressure
- thyroid disease
- diabetes
- trouble urinating due to an enlarged prostate gland
- glaucoma
- a breathing problem such as emphysema or chronic bronchitis

Ask a doctor or pharmacist before use if you are taking sedatives or tranquilizers.

When using this product

- do not use more than directed
- drowsiness may occur
- avoid alcoholic beverages
- alcohol, sedatives, and tranquilizers may increase drowsiness
- be careful when driving a motor vehicle or operating machinery
- excitability may occur, especially in children

Stop use and ask a doctor if

- you get nervous, dizzy, or sleepless
- symptoms do not get better within 7 days or are accompanied by fever

PREGNANCY OR BREAST FEEDING

If pregnant or breast-feeding, ask a health professional before use.

Keep out of reach of children. In case of overdose, get medical help.

Other information

- store at 20-25°C (68-77°F)
- not a USP elixir
- dosage cup provided
- Pleasant tasting – children find its great grape taste easy to take.
- Adults like it, too – especially those who have difficulty swallowing tablets or capsules.

Directions

- do not take more than 4 doses in any 24-hour period

age | dose
adults and children 12 years and over | 4 tsp every 4 hours
children 6 to under 12 years | 2 tsp every 4 hours
children under 6 years | Do not use

Inactive ingredients

artificial flavor, citric acid, FD&C blue no. 1, FD&C red no. 40, glycerin, high fructose corn syrup, propylene glycol, saccharin sodium, sodium benzoate, sorbitol, purified water

PRINCIPAL DISPLAY PANEL - 118 mL Bottle Carton

Dimetapp®
Elixir
NASAL DECONGESTANT
ANTIHISTAMINE

GREAT GRAPE TASTE
FOR CHILDREN & ADULTS

RELIEVES COLD AND
ALLERGY SYMPTOMS

NASAL CONGESTION

RUNNING NOSE

ITCHY, WATERY EYES

SNEEZING

4 FL. OZ. (118 mL)